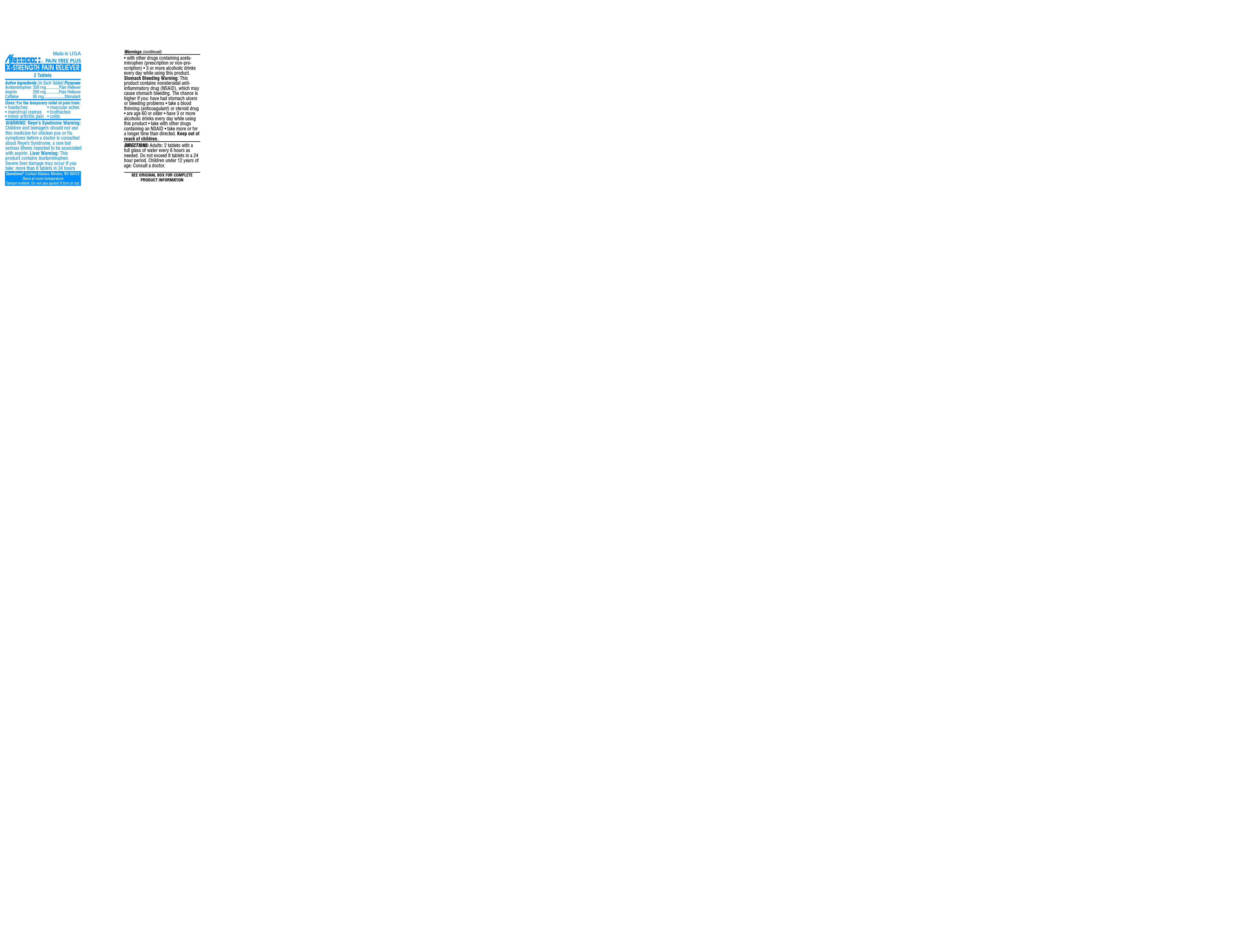 DRUG LABEL: Pain Free Plus
NDC: 51532-0560 | Form: TABLET
Manufacturer: Afassco Inc.
Category: otc | Type: HUMAN OTC DRUG LABEL
Date: 20190921

ACTIVE INGREDIENTS: ACETAMINOPHEN 250 1/1 1; ASPIRIN 250 1/1 1; CAFFEINE 65 1/1 1
INACTIVE INGREDIENTS: MICROCRYSTALLINE CELLULOSE; POVIDONE; SODIUM STARCH GLYCOLATE TYPE A CORN; STEARIC ACID; STARCH, CORN; HYPROMELLOSES; MALTODEXTRIN; POLYETHYLENE GLYCOL, UNSPECIFIED; TITANIUM DIOXIDE

Drug Facts

ACTIVE INGREDIENT

Acetaminophen 250mg, Aspirin 250mg, Caffeine 65mg

PURPOSE

Pin reliever, Stimulant

INDICATIONS AND USAGE

Uses: For the temporary relief of pain from:

• headaches • muscular aches

• menstrual cramps • toothaches

• minor arthritic pain • colds

WARNING:

Reye's Syndrome Warning: Children and teenagers should not use this medicine for chicken pox or flu symptoms before a doctor is consulted about Reye’s Syndrome, a rare but serious illness reported to be associated with aspirin.

Liver Warning: This product contains Acetaminophen. Severe liver damage may occur if you take: more than 8 tablets in 24 hours

• with other drugs containing acetaminophen (prescription or non-prescription)

• 3 or more alcoholic drinks every day while using this product.

Stomach Bleeding Warning: This product contains nonsteroidal antiinflammatory drug (NSAID), which may cause stomach bleeding. The chance is higher if you: have had stomach ulcers or bleeding problems • take a blood thinning (anticoagulant) or steroid drug

• are age 60 or older • have 3 or more alcoholic drinks every day while using this product • take with other drugs containing an NSAID • take more or for a longer time than directed.

Keep out of reach of children.

DIRECTIONS:

Adults: 2 tablets with a full glass of water every 6 hours as needed. Do not exceed 8 tablets in a 24 hour period.

Children under 12 years of age: Consult a doctor.

INACTIVE INGREDIENT

SEE ORIGINAL BOX FOR COMPLETE PRODUCT INFORMATION

PACKAGE LABEL

res